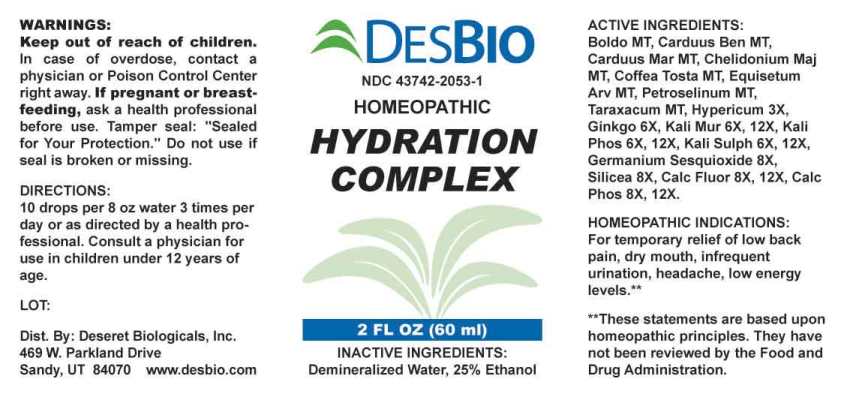 DRUG LABEL: Hydration Complex
NDC: 43742-2053 | Form: LIQUID
Manufacturer: Deseret Biologicals, Inc.
Category: homeopathic | Type: HUMAN OTC DRUG LABEL
Date: 20241004

ACTIVE INGREDIENTS: PEUMUS BOLDUS LEAF 1 [hp_X]/1 mL; CENTAUREA BENEDICTA 1 [hp_X]/1 mL; MILK THISTLE 1 [hp_X]/1 mL; CHELIDONIUM MAJUS WHOLE 1 [hp_X]/1 mL; COFFEA ARABICA SEED, ROASTED 1 [hp_X]/1 mL; EQUISETUM ARVENSE TOP 1 [hp_X]/1 mL; PETROSELINUM CRISPUM WHOLE 1 [hp_X]/1 mL; TARAXACUM OFFICINALE 1 [hp_X]/1 mL; HYPERICUM PERFORATUM WHOLE 3 [hp_X]/1 mL; GINKGO 6 [hp_X]/1 mL; POTASSIUM CHLORIDE 6 [hp_X]/1 mL; DIBASIC POTASSIUM PHOSPHATE 6 [hp_X]/1 mL; POTASSIUM SULFATE 6 [hp_X]/1 mL; GERMANIUM SESQUIOXIDE 8 [hp_X]/1 mL; SILICON DIOXIDE 8 [hp_X]/1 mL; CALCIUM FLUORIDE 8 [hp_X]/1 mL; TRIBASIC CALCIUM PHOSPHATE 8 [hp_X]/1 mL
INACTIVE INGREDIENTS: WATER; ALCOHOL

DRUG FACTS:

ACTIVE INGREDIENTS:

Boldo 1X, Carduus Benedictus 1X, Carduus Marianus 1X, Chelidonium Majus 1X, Coffea Tosta 1X, Equisetum Arvense 1X, Petroselinum Sativum 1X, Taraxacum Officinale 1X, Hypericum Perforatum 3X, Ginkgo Biloba 6X, Kali Muriaticum 6X, 12X, Kali Phosphoricum 6X, 12X, Kali Sulphuricum 6X, 12X, Germanium Sesquioxide 8X, Silicea 8X, Calcarea Fluorica 8X, 12X, Calcarea Phosphorica 8X, 12X.

HOMEOPATHIC INDICATIONS:

For temporary relief of low back pain, dry mouth, infrequent urination, headache, low energy levels.**

**These statements are based upon homeopathic principles. They have not been reviewed by the Food and Drug Administration.

WARNINGS:

Keep out of reach of children. In case of overdose, contact a physician or Poison Control Center right away.

If pregnant or breast-feeding, ask a health professional before use.

Tamper seal: "Sealed for Your Protection." Do not use if seal is broken or missing.

Keep out of reach of children. In case of overdose, contact a physician or Poison Control Center right away.

DIRECTIONS:

10 drops per 8 oz water 3 times per day or as directed by a health professional. Consult a physician for use in children under 12 years of age.

HOMEOPATHIC INDICATIONS:

For temporary relief of low back pain, dry mouth, infrequent urination, headache, low energy levels.**

**These statements are based upon homeopathic principles. They have not been reviewed by the Food and Drug Administration.

INACTIVE INGREDIENTS:

Demineralized Water, 25% Ethanol.

QUESTIONS:

Dist. By: Deseret Biologicals, Inc.

469 W. Parkland Drive

Sandy, UT 84070

www.desbio.com

PACKAGE LABEL DISPLAY:

DESBIO

NDC 43742-2053-1

HOMEOPATHIC

HYDRATION

COMPLEX

2 FL OZ (60 ml)